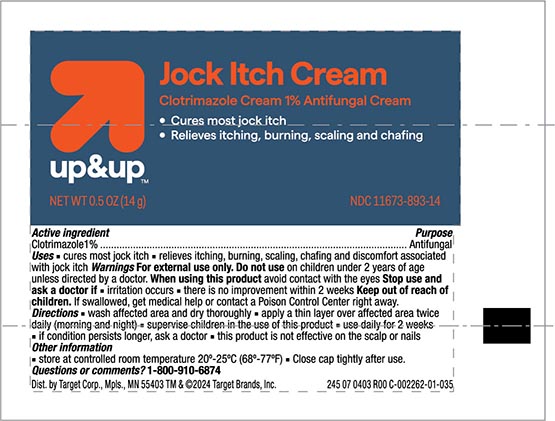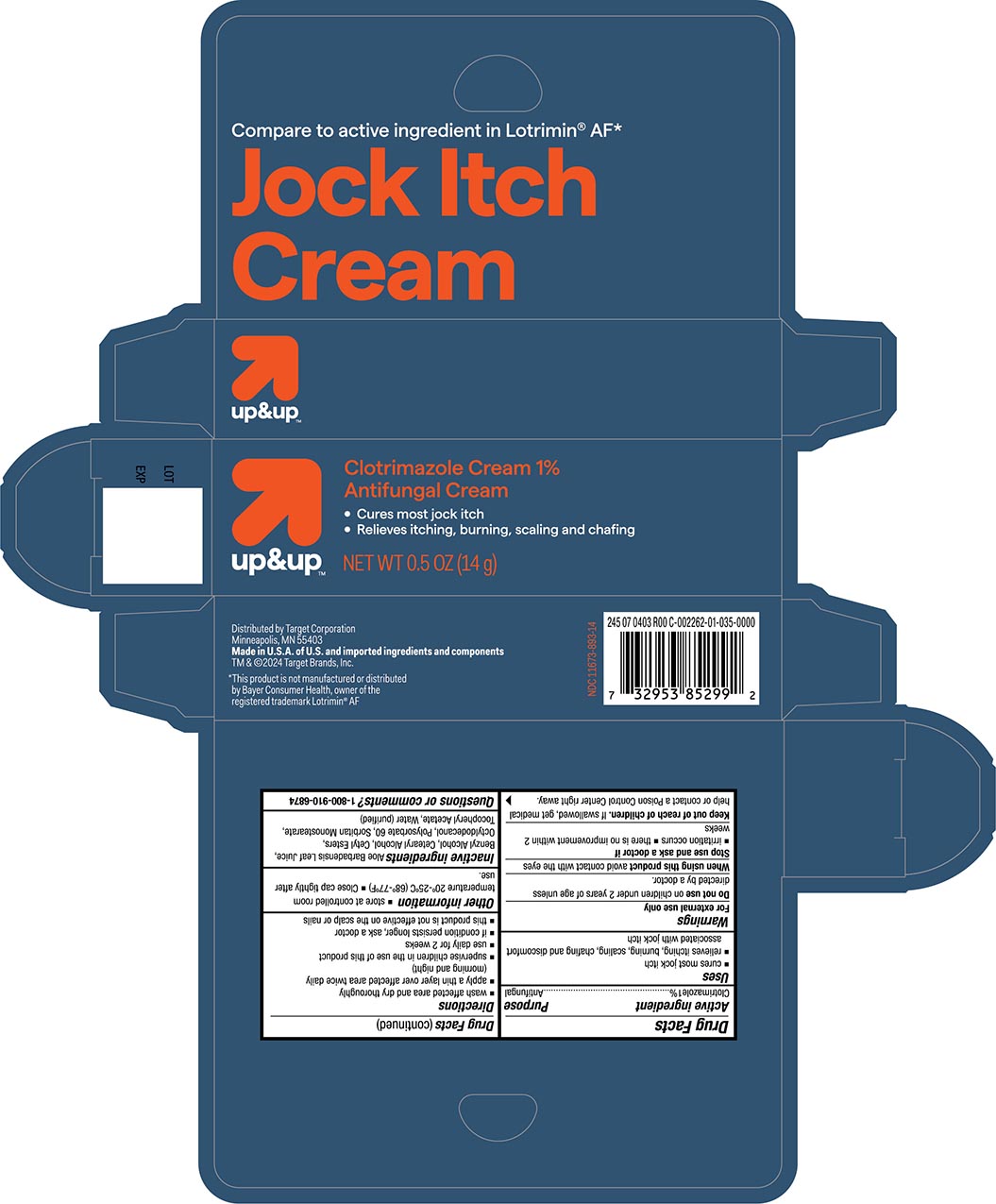 DRUG LABEL: Target Jock Itch
NDC: 11673-893 | Form: CREAM
Manufacturer: Target Corporation
Category: otc | Type: HUMAN OTC DRUG LABEL
Date: 20240117

ACTIVE INGREDIENTS: CLOTRIMAZOLE 10 mg/1 g
INACTIVE INGREDIENTS: ALOE VERA LEAF; BENZYL ALCOHOL; CETOSTEARYL ALCOHOL; CETYL ESTERS WAX; OCTYLDODECANOL; POLYSORBATE 80; SORBITAN MONOSTEARATE; .ALPHA.-TOCOPHEROL ACETATE; WATER

Target Up &Up Jock Itch Cream

Active

Clotrimazole 1%

Purpose

Antifungal

Uses

- Cures most jock itch
- Relieves the itching, burning, scaling, chafing and discomfort associated with jock itch

Warnings

For external use only

Do not use on children under 2 years of age unless directed by a doctor.
When using this product avoid contact with eyes.

Stop use and consult a doctor if

- irritation occurs
- if there is not improvement within 2 weeks

Keep out of the reach of children

if swallowed, get medical help or contact a poison control center right away.

Directions

- Wash the affected area and dry thoroughly.
- Apply a thin layer of this product over affected area twice daily (morning and night)
- Supervise children in the use of this product.
- use daily for 2 weeks.
- If conditions persist longer, consult a doctor.
- This product is not effective on the scalp or nails.

Other information

- Store at controlled room temperature 20°-25°C (68°-77°F).
- Close cap tightly after use.

Inactive ingredients

Aloe Barbadensis Leaf Juice, Benzyl Alcohol, Cetearyl Alcohol, Cetyl Esters, Octyldodecanol, Polysorbate 60, Sorbitan Monostearate, Tocopheryl Acetate, Purified Water.

Principal Display Panel

Target Up and Up NDC 11673-893-14

Jock itch Cream

Clotrimazole 1%

Antifungal Cream

NET WT 0.5OZ (14g)